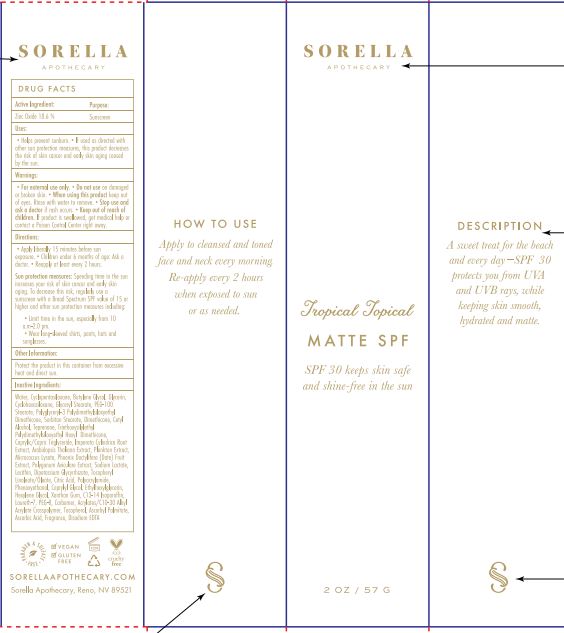 DRUG LABEL: Tropical Topical Matte SPF30
NDC: 62742-4231 | Form: CREAM
Manufacturer: Allure Labs
Category: otc | Type: HUMAN OTC DRUG LABEL
Date: 20241008

ACTIVE INGREDIENTS: ZINC OXIDE 18.6 g/100 g
INACTIVE INGREDIENTS: CYCLOMETHICONE 5; GLYCYRRHIZINATE DIPOTASSIUM; TOCOPHEROL; PHENOXYETHANOL; HEXYLENE GLYCOL; EDETATE DISODIUM ANHYDROUS; CETYL ALCOHOL; MEDIUM-CHAIN TRIGLYCERIDES; SORBITAN MONOSTEARATE; LECITHIN, SOYBEAN; ETHYLHEXYLGLYCERIN; ASCORBYL PALMITATE; PEG-100 STEARATE; POLYGLYCERYL-3 POLYDIMETHYLSILOXYETHYL DIMETHICONE (4000 MPA.S); MICROCOCCUS LUTEUS; POLYGONUM AVICULARE TOP; SODIUM LACTATE; LINOLEIC ACID; POLYACRYLAMIDE (CROSSLINKED; 2 MOLE PERCENT BISACRYLAMIDE); XANTHAN GUM; ASCORBIC ACID; ARABIDOPSIS THALIANA; TRIETHOXYSILYLETHYL POLYDIMETHYLSILOXYETHYL HEXYL DIMETHICONE; CYCLOMETHICONE 6; GLYCERYL MONOSTEARATE; DATE; POLYETHYLENE GLYCOL 400; C13-14 ISOPARAFFIN; CAPRYLYL GLYCOL; IMPERATA CYLINDRICA ROOT; CITRIC ACID MONOHYDRATE; CARBOMER HOMOPOLYMER, UNSPECIFIED TYPE; CARBOMER COPOLYMER TYPE B (ALLYL PENTAERYTHRITOL CROSSLINKED); WATER; BUTYLENE GLYCOL; LAURETH-7; GLYCERIN; TEPRENONE

Drug Facts

ACTIVE INGREDIENTS:
Zinc Oxide – 18.6 %

Purpose: Sunscreen

INDICATIONS AND USAGE

Uses: Helps prevent sunburn. If used as directed with other sun protection measures, this product decreases the risk of skin cancer and early skin aging caused by the sun.

Warning:

For external use only

Do not use on damage or broken skin.

When using this product keep out of eye. Rinse with water to remove.

Stop use and ask a doctor if rash occurs.

Keep out of reach of children if product is swallowed, get medical help or contact a poison control center right away.

DOSAGE AND ADMINISTRATION

Direction:

Apply liberally 15 minutes before sun exposure.

Children under 6 month of age: Ask a doctor

Reapply at least every 2 hours.

Sun protection measures: Spending time in the sun increases your risk of skin cancer and early skin aging. To decreases this risk regularly use a sunscreen with a broad spectrum SPF value of 15 or higher and other sun protection measures including: Limit time in the sun< especially from 10 am – 2.0 pm, Wear long – sleeved shirts, pants, hats and sunglasses.

Other Information:

Protect the product in this container from excessive heat and direct sun.

INACTIVE INGREDIENT: Water, Cyclopentasiloxane, Butylene Glycol, Glycerin, Cyclohexasiloxane, Glyceryl Stearate, PEG-100 Stearate, Polyglyceryl-3 Polydimethylsiloxyethyl, Dimethicone, Sorbitan Stearate, Cetyl Alcohol, Teprenone, Triethoxysilylethyl Polydimethylsiloxyethyl Hexyl Dimethicone, Caprylic/Capric Triglyceride, Imperata Cylendrica Root Extract, Arabidopsis Thaliana Extract, Plankton Extract, Micrococcus Lysate, Phoenix Dactylifera (Date) Fruit Extract, Polygonum Aviculare Extract, Sodium Lactate, Lecithin, Dipotassium Glycyrrhizate, Tocopheryl Linoleate/ Oleate, Citric Acid, Polyacrylamide, Phenoxyethanol, Caprylyl Glycol, Ethylhexylglycerine, Hexylene Glycol, Xanthan Gum, C13-14 Isoparaffin, Laureth-7, PEG-8, Carbomer, Acrylates/C10-30 Alkyl Acrylate Crosspolymer, Tocopherol, Asccorbyl Palmitate, Ascorbc Acid, Fragrance, Disodium EDTA.